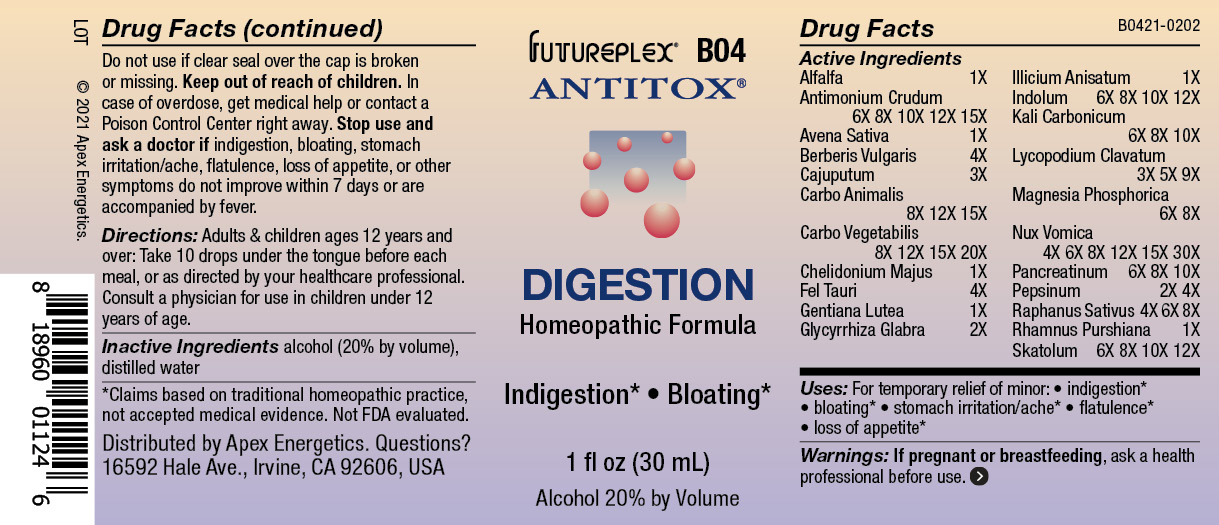 DRUG LABEL: B04
NDC: 63479-0204 | Form: SOLUTION/ DROPS
Manufacturer: Apex Energetics Inc.
Category: homeopathic | Type: HUMAN OTC DRUG LABEL
Date: 20240108

ACTIVE INGREDIENTS: PANCRELIPASE 10 [hp_X]/1 mL; PEPSIN 4 [hp_X]/1 mL; FRANGULA PURSHIANA BARK 1 [hp_X]/1 mL; GLYCYRRHIZA GLABRA 2 [hp_X]/1 mL; STAR ANISE 1 [hp_X]/1 mL; POTASSIUM CARBONATE 10 [hp_X]/1 mL; ACTIVATED CHARCOAL 20 [hp_X]/1 mL; BERBERIS VULGARIS ROOT BARK 4 [hp_X]/1 mL; CAJUPUT OIL 3 [hp_X]/1 mL; CARBO ANIMALIS 15 [hp_X]/1 mL; BOS TAURUS BILE 4 [hp_X]/1 mL; LYCOPODIUM CLAVATUM SPORE 9 [hp_X]/1 mL; MAGNESIUM PHOSPHATE, DIBASIC TRIHYDRATE 8 [hp_X]/1 mL; STRYCHNOS NUX-VOMICA SEED 30 [hp_X]/1 mL; GENTIANA LUTEA ROOT 1 [hp_X]/1 mL; INDOLE 12 [hp_X]/1 mL; SKATOLE 12 [hp_X]/1 mL; AVENA SATIVA FLOWERING TOP 1 [hp_X]/1 mL; CHELIDONIUM MAJUS 1 [hp_X]/1 mL; RADISH 8 [hp_X]/1 mL; ALFALFA 1 [hp_X]/1 mL; ANTIMONY TRISULFIDE 15 [hp_X]/1 mL
INACTIVE INGREDIENTS: WATER; ALCOHOL

B04

Active Ingredients
Alfalfa | 1X
Antimonium Crudum | 6X 8X 10X 12X 15X
Avena Sativa | 1X
Berberis Vulgaris | 4X
Cajuputum | 3X
Carbo Animalis | 8X 12X 15X
Carbo Vegetabilis | 8X 12X 15X 20X
Chelidonium Majus | 1X
Fel Tauri | 4X
Gentiana Lutea | 1X
Glycyrrhiza Glabra | 2X
Illicium Anisatum | 1X
Indolum | 6X 8X 10X 12X
Kali Carbonicum | 6X 8X 10X
Lycopodium Clavatum | 3X 5X 9X
Magnesia Phosphorica | 6X 8X
Nux Vomica | 4X 6X 8X 12X 15X 30X
Pancreatinum | 6X 8X 10X
Pepsinum | 2X 4X
Raphanus Sativus | 4X 6X 8X
Rhamnus Purshiana | 1X
Skatolum | 6X 8X 10X 12X

INDICATIONS AND USAGE

Uses:

For temporary relief of minor:

indigestion*

bloating*

stomach irritation/ache*

flatulence*

loss of appetite*

*Claims based on traditional homeopathic practice, not accepted medical evidence. Not FDA evaluated.

WARNINGS

PREGNANCY OR BREAST FEEDING

If pregnant or breastfeeding, ask a health professional before use.

Do not use if clear seal over the cap is broken or missing.

Keep out of reach of children. In case of overdose, get medical help or contact a Poison Control Center right away.

Stop use and ask a doctor if indigestion, bloating, stomach irritation/ache, flatulence, loss of appetite, or other symptoms do not improve within 7 days or are accompanied by fever.

Directions:

Adults & children ages 12 years and over: Take 10 drops under the tongue before each meal, or as directed by your healthcare professional. Consult a physician for use in children under 12 years of age.

Inactive Ingredients

alcohol (20% by volume), distilled water

Distributed by Apex Energetics. Questions?

16592 Hale Ave., Irvine, CA 92606, USA

PACKAGE LABEL

FUTUREPLEX® B04

ANTITOX®

DIGESTION

Homeopathic Formula

Indigestion*

Bloating*

1 fl oz (30 mL)

Alcohol 20% by Volume